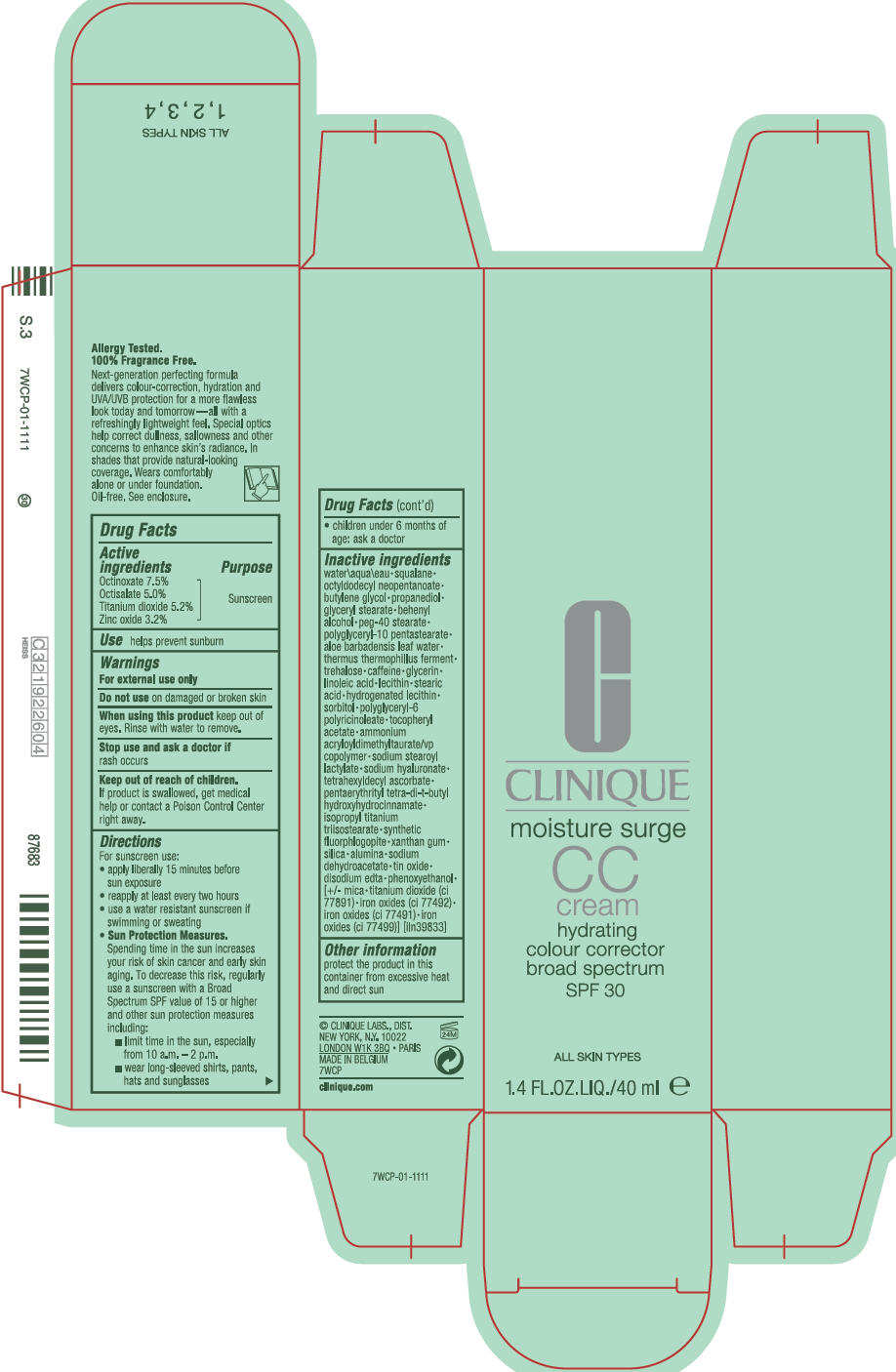 DRUG LABEL: MOISTURE SURGE CC
NDC: 49527-029 | Form: CREAM
Manufacturer: CLINIQUE LABORATORIES LLC
Category: otc | Type: HUMAN OTC DRUG LABEL
Date: 20250815

ACTIVE INGREDIENTS: OCTINOXATE 75 mg/1 mL; OCTISALATE 50 mg/1 mL; TITANIUM DIOXIDE 52 mg/1 mL; ZINC OXIDE 32 mg/1 mL
INACTIVE INGREDIENTS: MICA; FERRIC OXIDE YELLOW; FERRIC OXIDE RED; FERROSOFERRIC OXIDE; LECITHIN, SOYBEAN; POLYGLYCERYL-6 POLYRICINOLEATE; MAGNESIUM POTASSIUM ALUMINOSILICATE FLUORIDE; THERMUS THERMOPHILUS LYSATE; POLYGLYCERYL-10 PENTASTEARATE; WATER; SQUALANE; OCTYLDODECYL NEOPENTANOATE; BUTYLENE GLYCOL; PROPANEDIOL; GLYCERYL MONOSTEARATE; DOCOSANOL; PEG-40 STEARATE; ALOE VERA LEAF; TREHALOSE; CAFFEINE; GLYCERIN; LINOLEIC ACID; STEARIC ACID; SORBITOL; .ALPHA.-TOCOPHEROL ACETATE; AMMONIUM ACRYLOYLDIMETHYLTAURATE/VP COPOLYMER; SODIUM STEAROYL LACTYLATE; HYALURONATE SODIUM; TETRAHEXYLDECYL ASCORBATE; PENTAERYTHRITOL TETRAKIS(3-(3,5-DI-TERT-BUTYL-4-HYDROXYPHENYL)PROPIONATE); ISOPROPYL TITANIUM TRIISOSTEARATE; XANTHAN GUM; SILICON DIOXIDE; ALUMINUM OXIDE; SODIUM DEHYDROACETATE; STANNIC OXIDE; EDETATE DISODIUM; PHENOXYETHANOL

MOISTURE SURGE CC
BROAD SPECTRUM SPF 30 HYDRATING COLOUR CORRECTOR

Drug Facts

Active ingredients

Octinoxate 7.5%
Octisalate 5.0%
Titanium dioxide 5.2%
Zinc oxide 3.2%

Purpose

Sunscreen

Use

helps prevent sunburn

Warnings

For external use only

Do not use on damaged or broken skin

When using this product keep out of eyes. Rinse with water to remove.

Stop use and ask a doctor if rash occurs

Keep out of reach of children. If product is swallowed, get medical help or contact a Poison Control Center right away.

Directions

For sunscreen use:

- apply liberally 15 minutes before sun exposure
- reapply at least every two hours
- use a water resistant sunscreen if swimming or sweating
- Sun Protection Measures.
  Spending time in the sun increases your risk of skin cancer and early skin aging. To decrease this risk, regularly use a sunscreen with a Broad Spectrum SPF value of 15 or higher and other sun protection measures including:
  - limit time in the sun, especially from 10 a.m. – 2 p.m.
  - wear long-sleeved shirts, pants, hats and sunglasses
- children under 6 months of age: ask a doctor

Inactive ingredients

water\aqua\eau • squalane • octyldodecyl neopentanoate • butylene glycol • propanediol • glyceryl stearate • behenyl alcohol • peg-40 stearate • polyglyceryl-10 pentastearate • aloe barbadensis leaf water • thermus thermophillus ferment • trehalose • caffeine • glycerin • linoleic acid • lecithin • stearic acid • hydrogenated lecithin • sorbitol • polyglyceryl-6 polyricinoleate • tocopheryl acetate • ammonium acryloyldimethyltaurate/vp copolymer • sodium stearoyl lactylate • sodium hyaluronate • tetrahexyldecyl ascorbate • pentaerythrityl tetra-di-t-butyl hydroxyhydrocinnamate • isopropyl titanium triisostearate • synthetic fluorphlogopite • xanthan gum • silica • alumina • sodium dehydroacetate • tin oxide • disodium edta • phenoxyethanol • [+/- mica • titanium dioxide (ci 77891) • iron oxides (ci 77492) • iron oxides (ci 77491) • iron oxides (ci 7799)] [iln39833]

Other information

protect the product in this container from excessive heat and direct sun

CLINIQUE LABS., DIST.
NEW YORK, N.Y. 10022

PRINCIPAL DISPLAY PANEL - 40 ml Bottle Carton

C

CLINIQUE

moisture surge
CC
cream
hydrating
colour corrector
broad spectrum
SPF 30

ALL SKIN TYPES

1.4 FL.OZ.LIQ./40 ml e